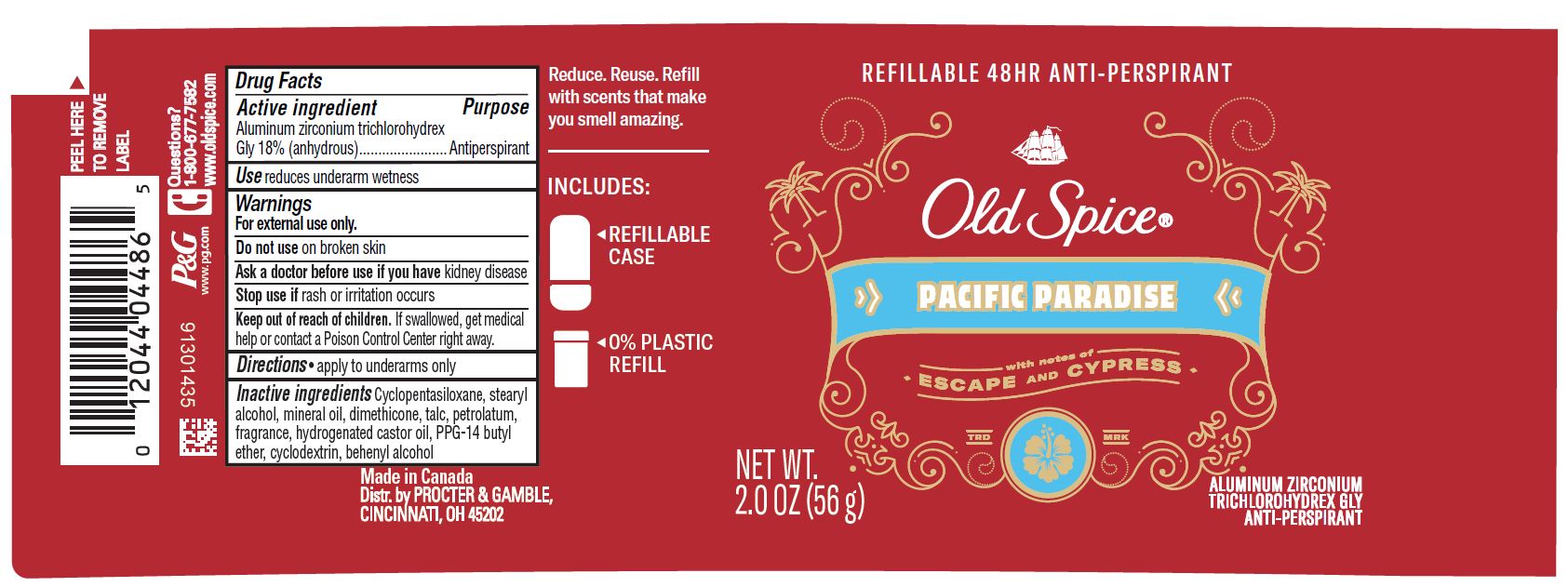 DRUG LABEL: Old Spice Pacific Paradise Refillable
NDC: 69423-493 | Form: STICK
Manufacturer: The Procter & Gamble Manufacturing Company
Category: otc | Type: HUMAN OTC DRUG LABEL
Date: 20201202

ACTIVE INGREDIENTS: ALUMINUM ZIRCONIUM TRICHLOROHYDREX GLY 18 g/100 g
INACTIVE INGREDIENTS: BETADEX; DIMETHICONE; HYDROGENATED CASTOR OIL; CYCLOMETHICONE 5; STEARYL ALCOHOL; PPG-14 BUTYL ETHER; PETROLATUM; TALC; MINERAL OIL; DOCOSANOL

Old Spice® Pacific Paradise Refillable

Drug Facts

Active ingredient

Aluminum zirconium trichlorohydrex Gly 18% (anhydrous)

Purpose

Antiperspirant

Use

reduces underarm wetness

Warnings

For external use only.

Do not use on broken skin

Ask a doctor before use if you have kidney disease

Stop use if rash or irritation occurs

Keep out of reach of children.

If swallowed, get medical help or contact a Poison Control Center right away.

Directions

- apply to underarms only

Inactive ingredients

cyclopentasiloxane, stearyl alcohol, mineral oil, dimethicone, talc, petrolatum, fragrance, hydrogenated castor oil, PPG-14 butyl ether, cyclodextrin, behenyl alcohol

Questions?

1-800-677-7582

Dist. by PROCTER & GAMBLE,
CINCINNATI, OH 45202.

PRINCIPAL DISPLAY PANEL - 56g Canister Label

REFILLABLE 48HR ANTI-PERSPIRANT

Old Spice

PACIFIC PARADISE

ALUMINUM ZIRCONIUM

TRICHLOROHYDREX GLY

ANTI-PERSPIRANT

NET WT.

2.0 OZ (56 g)